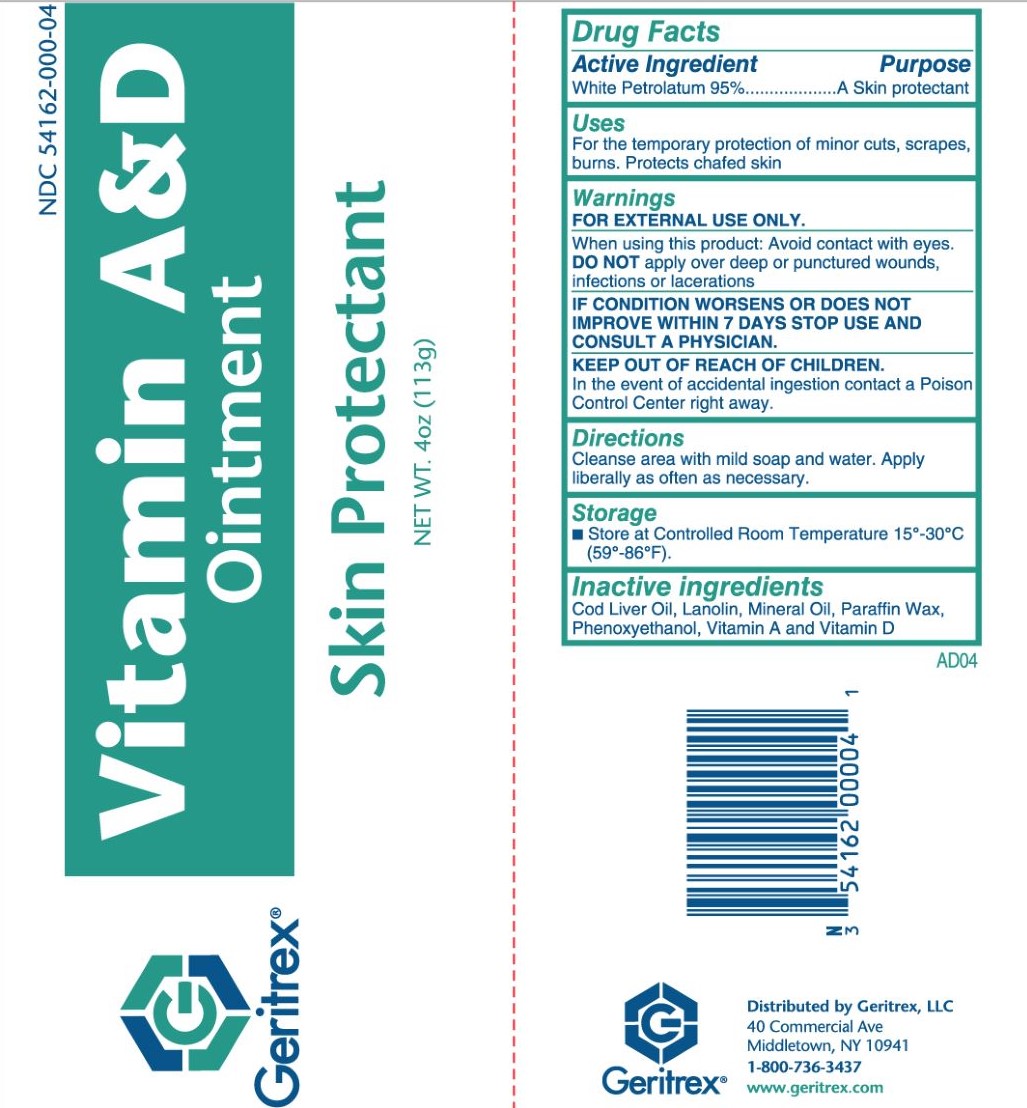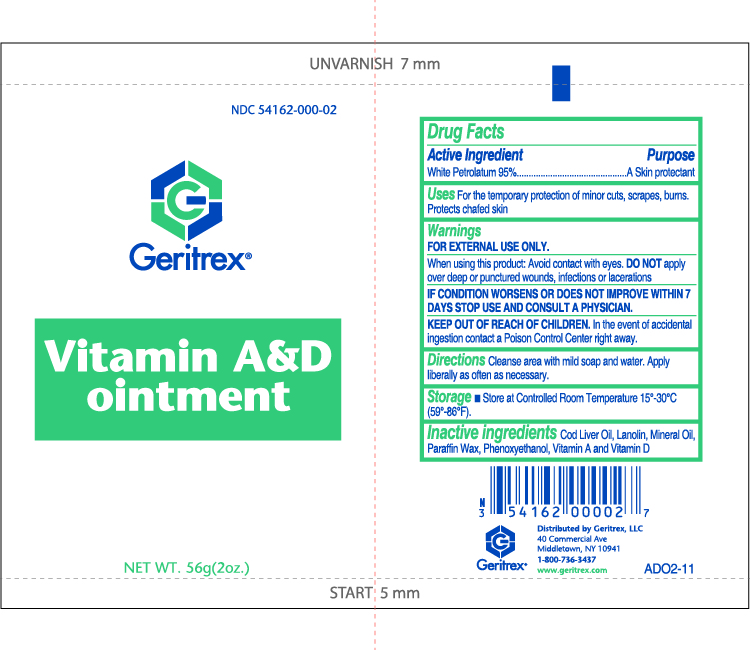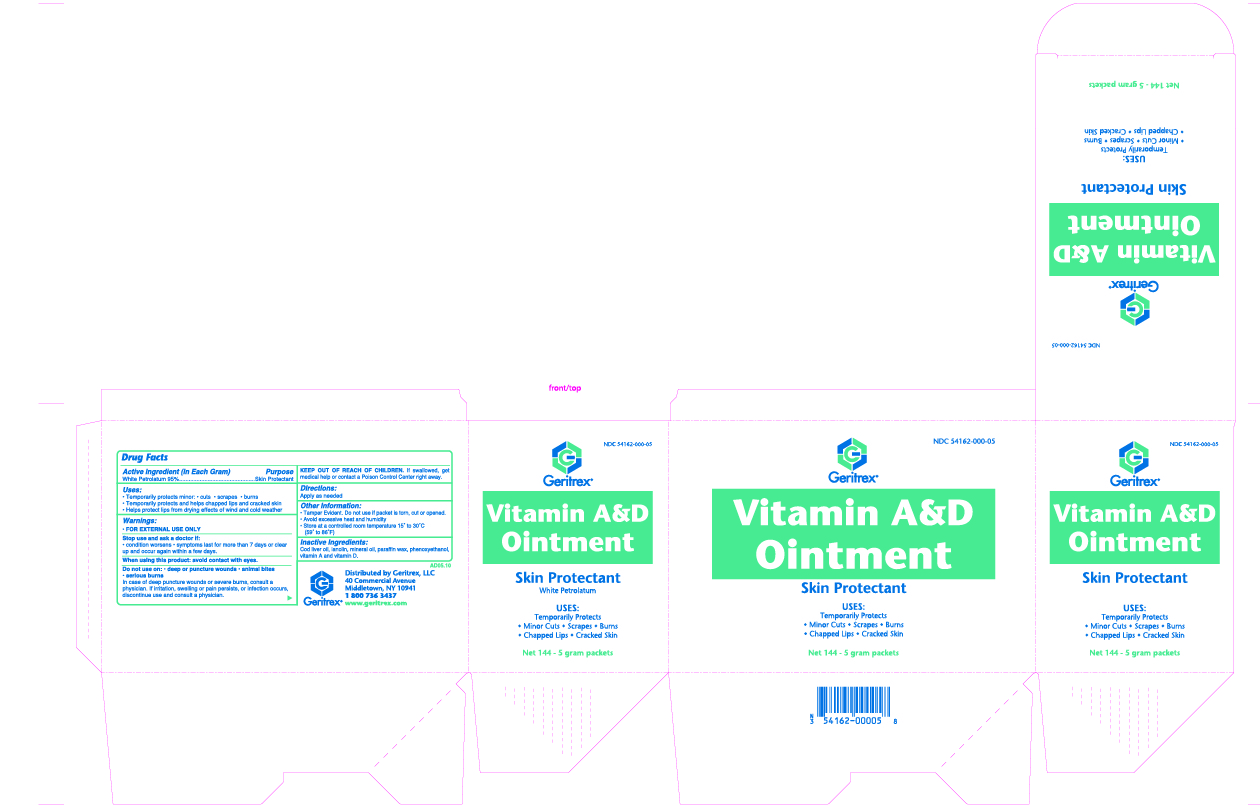 DRUG LABEL: Vitamin A and D
NDC: 54162-000 | Form: OINTMENT
Manufacturer: GERITREX LLC
Category: otc | Type: HUMAN OTC DRUG LABEL
Date: 20181012

ACTIVE INGREDIENTS: PETROLATUM 30.8 g/56 g
INACTIVE INGREDIENTS: COD LIVER OIL; LANOLIN; LIGHT MINERAL OIL; PARAFFIN; PHENOXYETHANOL; VITAMIN A; VITAMIN D

Vitamin A&D Ointment

Active Ingredient

White Petrolatum 95%

Purpose

A Skin protectant

Uses

For the temporary protection of minor cuts, scrapes, burns. Protects chafed skin

Warnings

FOR EXTERNAL USE ONLY.

When using this product: Avoid contact with eyes.

DO NOT apply over deep or punctured wounds, infections or lacerations

IF CONDITION WORSENS OR DOES NOT
IMPROVE WITHIN 7 DAYS STOP USE AND
CONSULT A PHYSICIAN.

KEEP OUT OF REACH OF CHILDREN.

In the event of accidental ingestion contact a Poison Control Center right away.

Directions

Cleanse area with mild soap and water. Apply liberally as often as necessary.

Storage

- Store at Controlled Room Temperature 15°-30°C (59°-86°F).

Inactive ingredients

Cod Liver Oil, Lanolin, Mineral Oil, Paraffin Wax, Phenoxyethanol, Vitamin A and Vitamin D